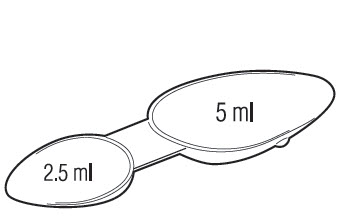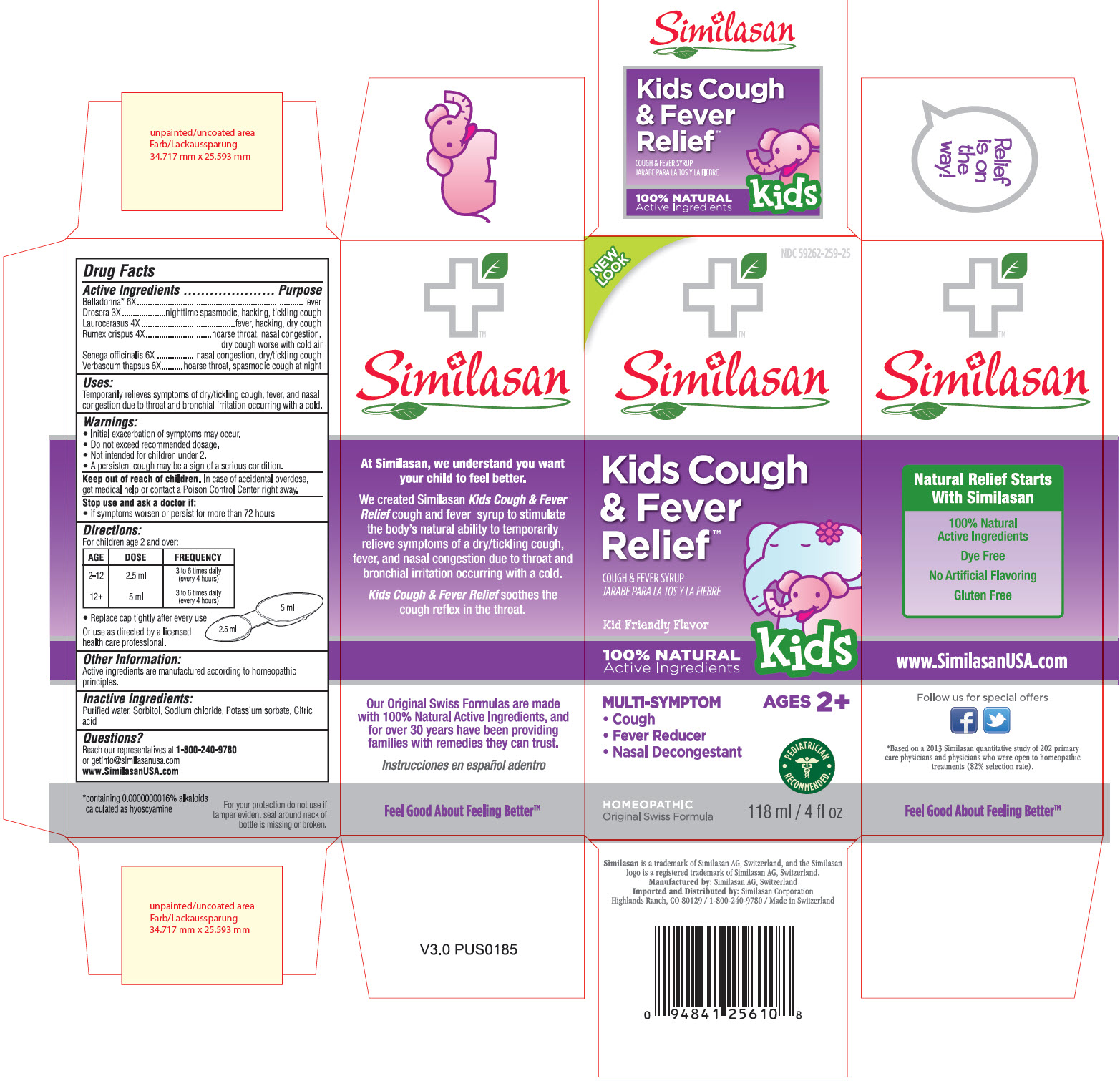 DRUG LABEL: Kids Cough and Fever Relief
NDC: 59262-259 | Form: SYRUP
Manufacturer: Similasan Corporation
Category: homeopathic | Type: HUMAN OTC DRUG LABEL
Date: 20130708

ACTIVE INGREDIENTS: ATROPA BELLADONNA 6 [hp_X]/118 mL; DROSERA ROTUNDIFOLIA 3 [hp_X]/118 mL; PRUNUS LAUROCERASUS LEAF 4 [hp_X]/118 mL; RUMEX CRISPUS ROOT 4 [hp_X]/118 mL; POLYGALA SENEGA ROOT 6 [hp_X]/118 mL; VERBASCUM THAPSUS 6 [hp_X]/118 mL
INACTIVE INGREDIENTS: WATER; SORBITOL; SODIUM CHLORIDE; POTASSIUM SORBATE; CITRIC ACID MONOHYDRATE

Kids Cough and Fever Relief

Active Ingredient

Belladonna* 6X
* containing 0.0000000016% alkaloids conculated as hyoscyamine

Purpose

fever

Active Ingredient

Drosera 3X

Purpose

nighttime spasmodic, hacking, tickling cough

Active Ingredient

Laurocerasus 4X

Purpose

fever, hacking, dry cough

Active Ingredient

Rumex crispus 4X

Purpose

hoarse throat, nasal congestion, dry cough worse with cold air

Active Ingredient

Senega officinalis 6X

Purpose

nasal congestion, dry/tickling cough

Active Ingredient

Verbascum thapsus 6X

Purpose

hoarse throat, spasmodic cough at night

Uses:

Temporarily relieves symptoms of dry/tickling cough, fever, and nasal congestion due to throat and bronchial irritation occurring with a cold.

Warnings

- Initial exacerbation of symptoms may occur.
- Do not exceed recommended dosage.
- Not intended for children under 2.
- A persistent cough may be a sign of a serious condition.

Keep out of reach of children.

In case of accidental overdose, get medical help or contact a Poison Control Center right away.

Stop use and ask a doctor if:

- if symptoms worsen or persist for more than 72 hours

Directions:

For children age 2 and over:

AGE | DOSE | FREQUENCY
2-12 | 2.5 ml | 3 to 6 times daily (every 4 hours)
12+ | 5 ml | 3 to 6 times daily (every 4 hours)

- Replace cap tightly after every use

Or use as directed by a licensed health care professional.

Other Information:

Active ingredients are manufactured according to homeopathic principles.

Inactive Ingredients:

Purified water, Sorbitol, Sodium chloride, Potassium sorbate, Citric acid

Questions?

Reach our representatives at 1-800-240-9780
or getinfo@similasanusa.com
www.SimilasanUSA.com

Principal Display Panel

NDC 59262-259-25
Similasan
Kids Cough & Fever Relief
Cough & Fever Syrup
118 ml / 4fl oz